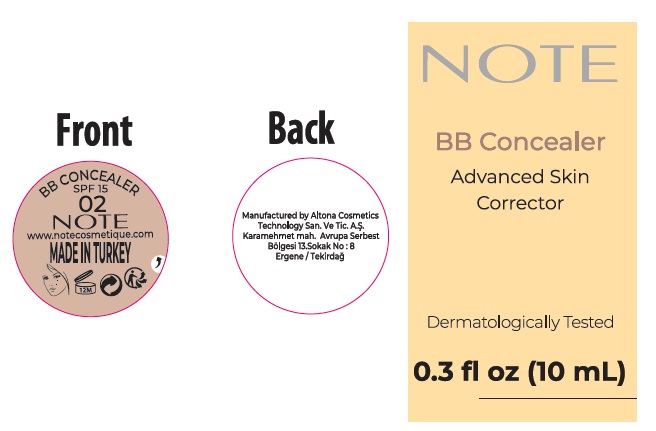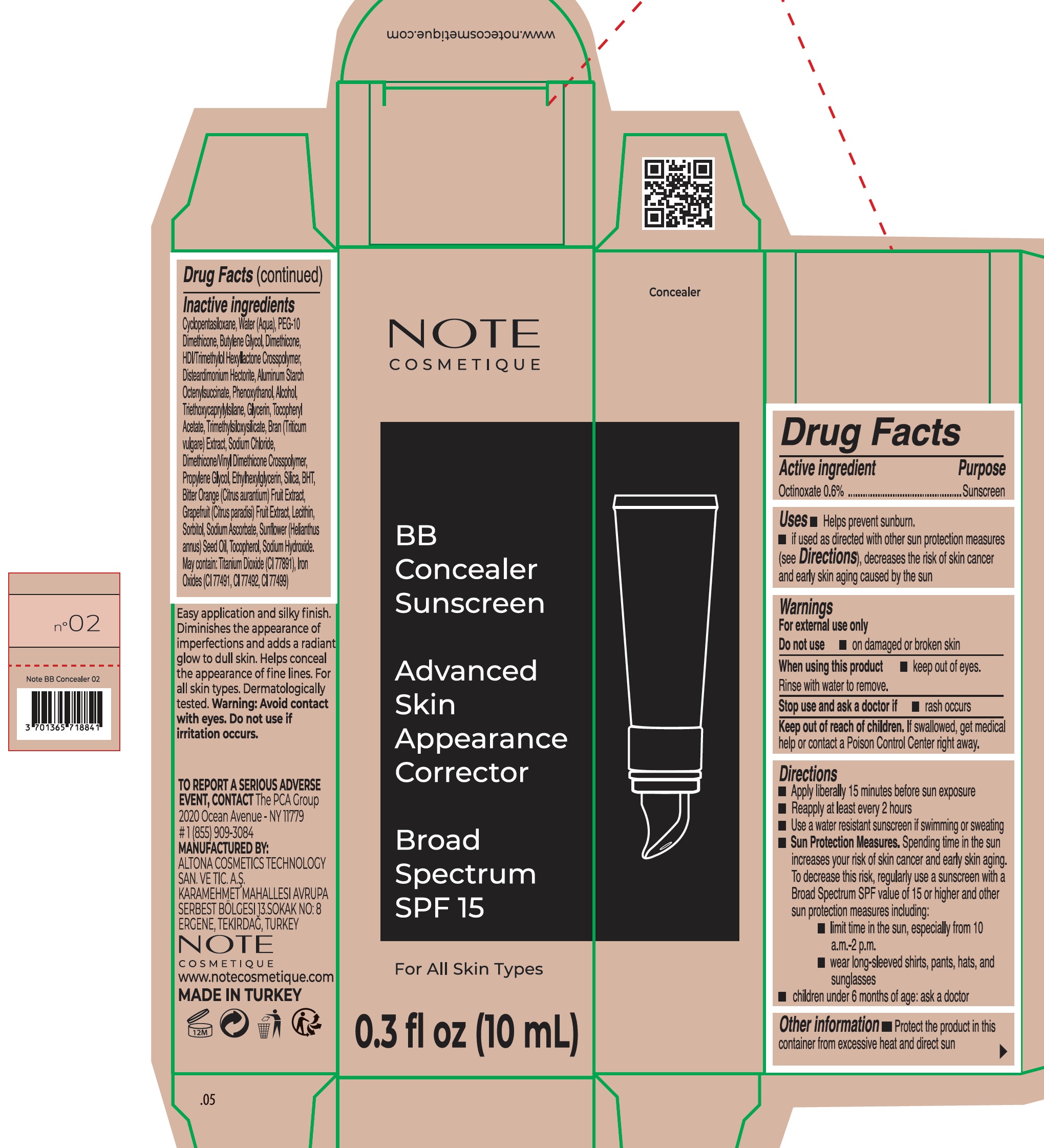 DRUG LABEL: Note BB Concealer 02
NDC: 70474-016 | Form: CREAM
Manufacturer: ALTONA COSMETICS TECHNOLOGY SANAYI VE TICARET ANONIM SIRKETI
Category: otc | Type: HUMAN OTC DRUG LABEL
Date: 20240916

ACTIVE INGREDIENTS: OCTINOXATE 6 mg/1 mL
INACTIVE INGREDIENTS: CYCLOMETHICONE 5; WATER; BUTYLENE GLYCOL; DIMETHICONE, UNSPECIFIED; HEXAMETHYLENE DIISOCYANATE/TRIMETHYLOL HEXYLLACTONE CROSSPOLYMER; DISTEARDIMONIUM HECTORITE; ALUMINUM STARCH OCTENYLSUCCINATE; PHENOXYETHANOL; ALCOHOL; TRIETHOXYCAPRYLYLSILANE; GLYCERIN; .ALPHA.-TOCOPHEROL ACETATE; SODIUM CHLORIDE; PROPYLENE GLYCOL; ETHYLHEXYLGLYCERIN; SILICON DIOXIDE; BUTYLATED HYDROXYTOLUENE; BITTER ORANGE; SORBITOL; SODIUM ASCORBATE; SUNFLOWER OIL; TOCOPHEROL; SODIUM HYDROXIDE; GRAPEFRUIT; WHEAT

Note BB Concealer Sunscreen SPF 15, 02

Active ingredient

Octinoxate 0.6%

Purpose

Sunscreen

Uses

- helps prevent sunburn
- if used as directed with other sun protection measures (see Directions), decreases the risk of skin cancer and early skin aging caused by the sun

Warnings

For external use only

Do not use

- on damaged or broken skin

When using this product

- keep out of eyes. Rinse with water to remove.

Stop use and ask a doctor if

- rash occurs.

Keep out of reach of children.

If swallowed, get medical help or contact a Poison Control Center right away.

Directions

- Apply liberally 15 minutes before sun exposure
- Reapply at least every 2 hours
- Use a water resistant sunscreen if swimming or sweating
- Sun Protection Measures. Spending time in the sun increases your risk of skin cancer and early skin aging. To decrease this risk, regularly use a sunscreen with a Broad Spectrum SPF value of 15 or higher and other sun protection measures including:
- limit time in the sun, especially from 10 a.m.-2 p.m.
- wear long-sleeved shirts, pants, hats, and sunglasses
- children under 6 months of age: Ask a doctor

Other information

- Protect the product in this container from excessive heat and direct sun

Inactive ingredients

Cyclopentasiloxane, Water (Aqua), PEG-10 Dimethicone, Butylene Glycol, Dimethicone, HDI/Trimethylol Hexyllactone Crosspolymer, Disteardimonium Hectorite, Aluminum Starch Octenylsuccinate, Phenoxyethanol, Alcohol, Triethoxycaprylylsilane, Glycerin, Tocopheryl Acetate, Trimethylsiloxysilicate, Bran (Triticum vulgare) Extract, Sodium Chloride, Dimethicone/Vinyl Dimethicone Crosspolymer, Propylene Glycol, Ethylhexylglycerin, Silica, BHT, Bitter Orange(Citrus aurantium) Fruit Extract, Grapefruit (Citrus paradisi) Fruit Extract, Lecithin, Sorbitol, Sodium Ascorbate, Sunflower (Helianthus annus) Seed Oil, Tocopherol, Sodium Hydroxide. May contain: Titanium Dioxide (CI 77891), Iron Oxides (CI 77491, CI 77492, CI 77499)